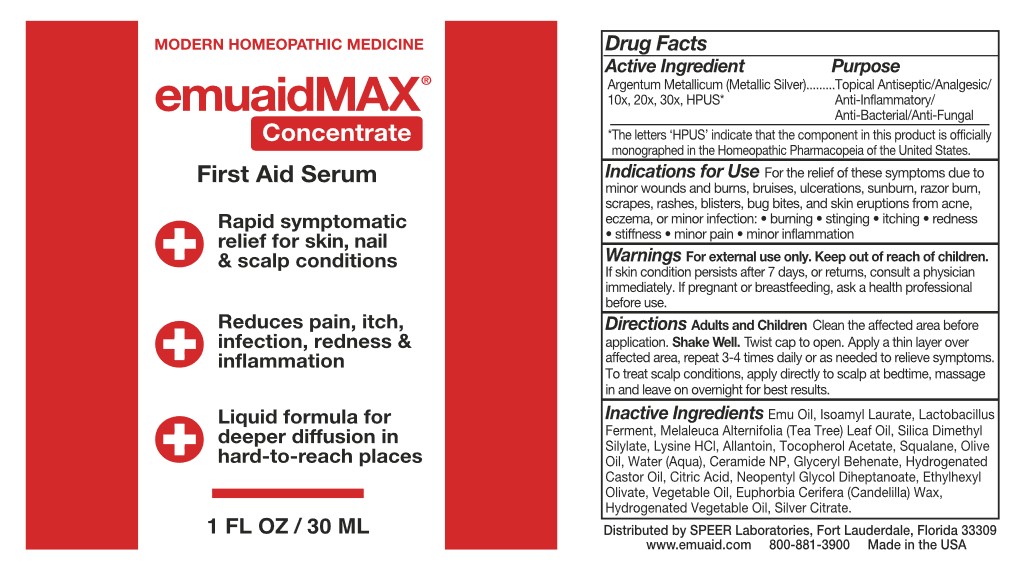 DRUG LABEL: emuaidMAX Concentrate
NDC: 55926-0027 | Form: LIQUID
Manufacturer: Speer Laboratories, LLC
Category: homeopathic | Type: HUMAN OTC DRUG LABEL
Date: 20231113

ACTIVE INGREDIENTS: silver 10 [hp_X]/100 mL
INACTIVE INGREDIENTS: EMU OIL; ISOAMYL LAURATE; LIMOSILACTOBACILLUS REUTERI; MELALEUCA ALTERNIFOLIA (TEA TREE) LEAF OIL; SILICA DIMETHYL SILYLATE; LYSINE HYDROCHLORIDE; ALLANTOIN; .ALPHA.-TOCOPHEROL ACETATE; SQUALANE; OLIVE OIL; WATER; CERAMIDE NP; GLYCERYL DIBEHENATE; HYDROGENATED CASTOR OIL; CITRIC ACID MONOHYDRATE; NEOPENTYL GLYCOL DIHEPTANOATE; ETHYLHEXYL OLIVATE; SOYBEAN OIL; PALM OIL; CANOLA OIL; CANDELILLA WAX; SILVER CITRATE

Active Ingredient

Argentum Metallicum (Metallic Silver) 10x, 20x, 30x, HPUS*

*The letters 'HPUS' indicate that the component in this product is offically monographed in the Homeopathic PHarmacopeia of the United States

Purpose

Topical Antiseptic/Analgesic/Anti-Inflammatory/Anti-Bacterial/Anti-Fungal

Indications for Use

For the relief of these symptoms due to minor wounds and burns, bruises, ulcerations, sunburn, razor burn, scrapes, rashes, blisters, bug bites, and skin eruptions from acne, eczema, or minor infection:
• burning • stinging • itching • redness • stiffness • minor pain • minor inflammation

Warnings

For external use only. If skin condition persists after 7 days, or returns, consult a physician immediately. If pregnant or breastfeeding, as a health professional before use.

Keep out of reach of children.

Directions

Adults and Children Clean the affected area before application. Shake well.
Twist cap to open. Apply a thin layer over affected area, repeat 3-4 times daily or as needed ot relieve symptoms.
To treat scalp conditions, apply directly to scalp at bedtime, massage in and leave on overnight for best results.

Inactive Ingredients

Emu Oil, Isoamyl Laurate, Lactobacillus Ferment, Melaleuca Alternifolia (Tea Tree) Leaf Oil, Silica Dimethyl Silylate, Lysine HCl, Allantoin, Tocophyeryl Acetate, Squalane, Olive Oil, Water, Ceramine NP, Glyceryl Behenate, Hydrogenated Castor Oil,
Citric Acid, Neopentyl Glycol Diheptanoate, Ethylhexyl Olivate, Vegetable Oil, Hydrogenated Vegetable Oil, Euphorbia Cerifera (Candella) Wax, Silver Citrate

Distributed by SPEER Laboratories, Ft. Lauderdale, Florida, 33309
www.emuaid.com
800-881-3900
Made in USA

PACKAGE LABEL

Modern Homeopathic Medicine
emuaidMAX(R) Concentrate

First Aid Serum

Rapid symptomatic relief for skin, nail & scalp conditions
Reduces pain, itch, infection, redness & inflammation
Liquid formula for deeper diffusion in hard-to-reach places

1 FL OZ / 30 ML